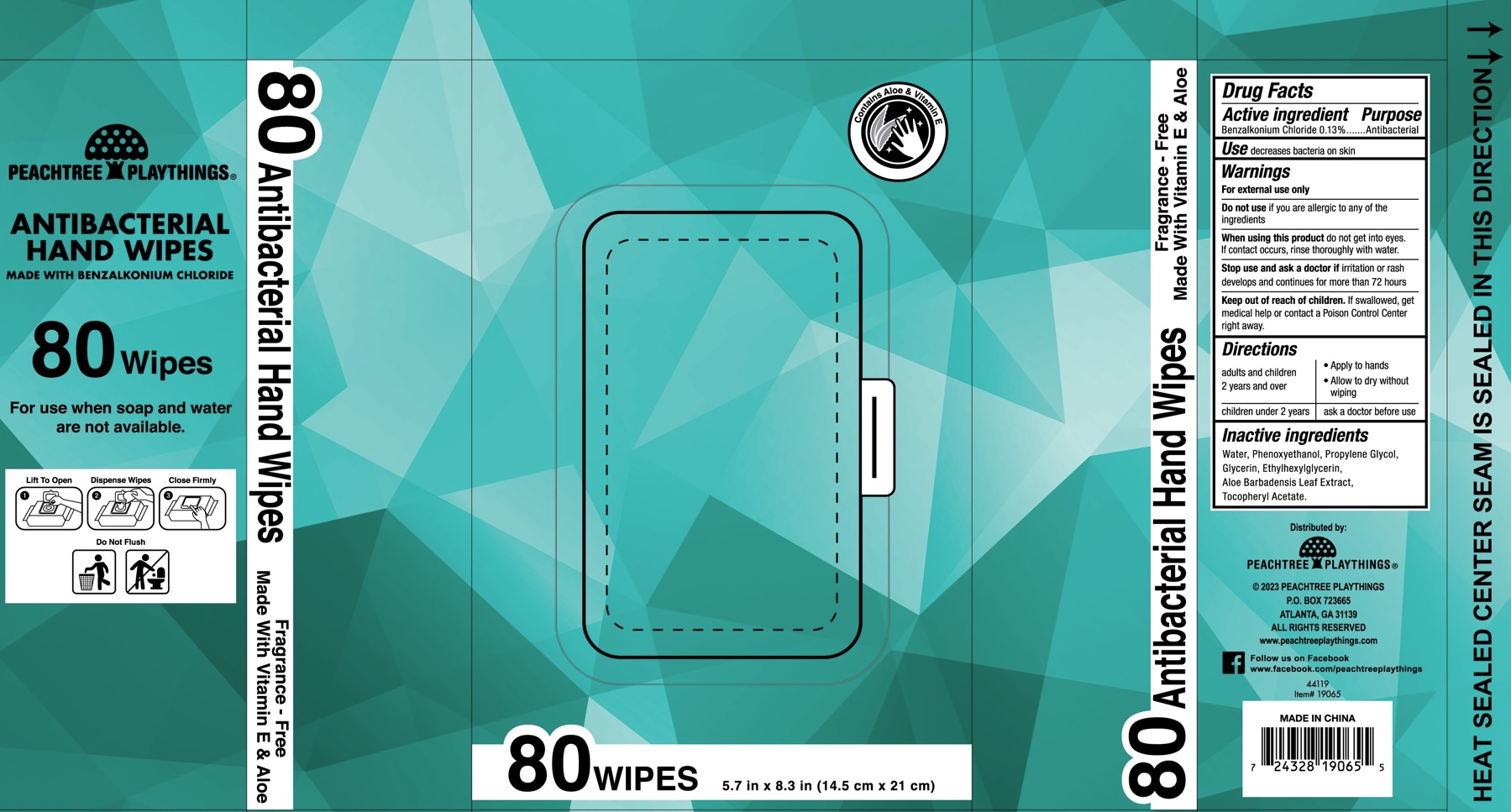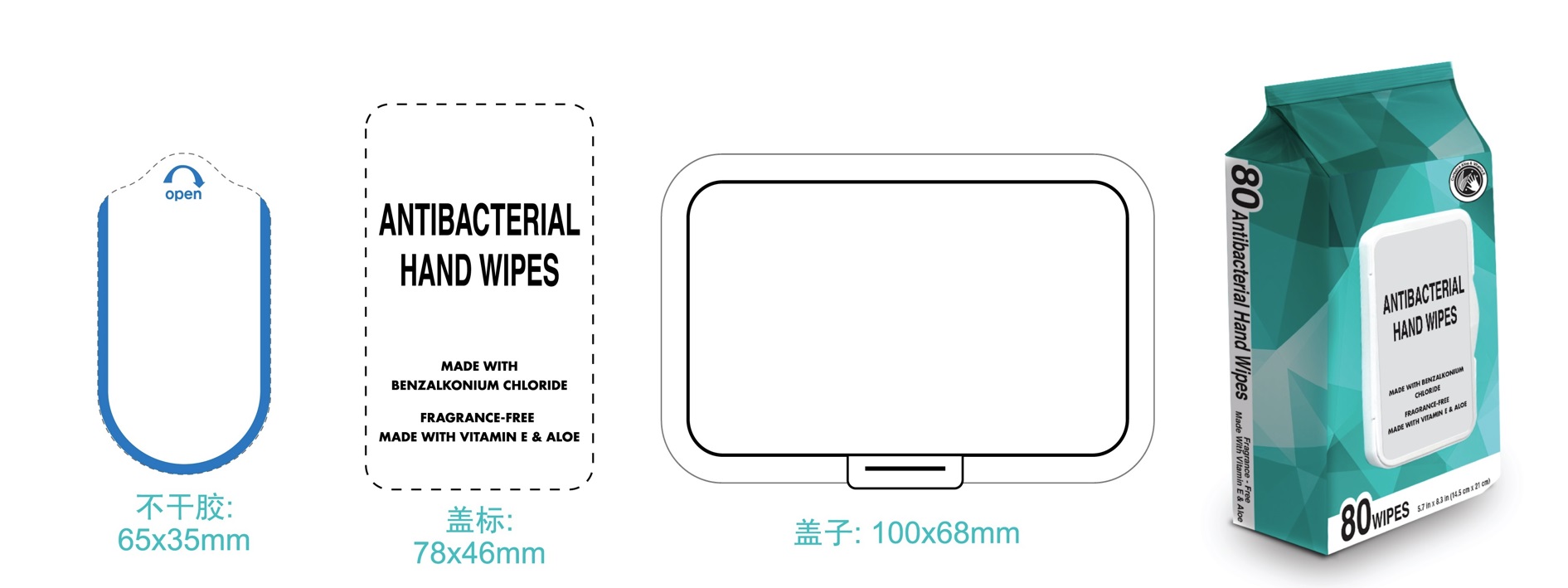 DRUG LABEL: Antibacterial Hand Wipes
NDC: 44119-012 | Form: CLOTH
Manufacturer: Peachtree Playthings, Inc.
Category: otc | Type: HUMAN OTC DRUG LABEL
Date: 20250820

ACTIVE INGREDIENTS: BENZALKONIUM CHLORIDE 1.3 mg/1 mL
INACTIVE INGREDIENTS: WATER; PHENOXYETHANOL; PROPYLENE GLYCOL; GLYCERIN; ETHYLHEXYLGLYCERIN; ALOE VERA LEAF; .ALPHA.-TOCOPHEROL ACETATE

Antibacterial Hand Wipes

Active ingredient

Benzalkonium Chloride 0.13%

Purpose

Antibacterial

Use

decreases bacteria on skin

Warnings

For external use only

Do not use

if you are allergic to any ingredients

When using this product

do not get into your eyes. If contact occurs, rinse thoroughly with water.

Stop use and ask a doctor if

irritation or rash develops and continues for more than 72 hours.

KEEP OUT OF REACH OF CHILDREN

If swallowed, get medical help or contact a Poison Control Center right away.

Directions

adults and children 2 years and over | - Apply to hands - Allow to dry without wiping
children under 2 years | ask a doctor before use

Inactive ingredients

Water, Phenoxyethanol, Propylene Glycol, Glycerin, Ethylhexylglycerin, Aloe Barbadensis Leaf Extract, Tocopheryl Acetate.